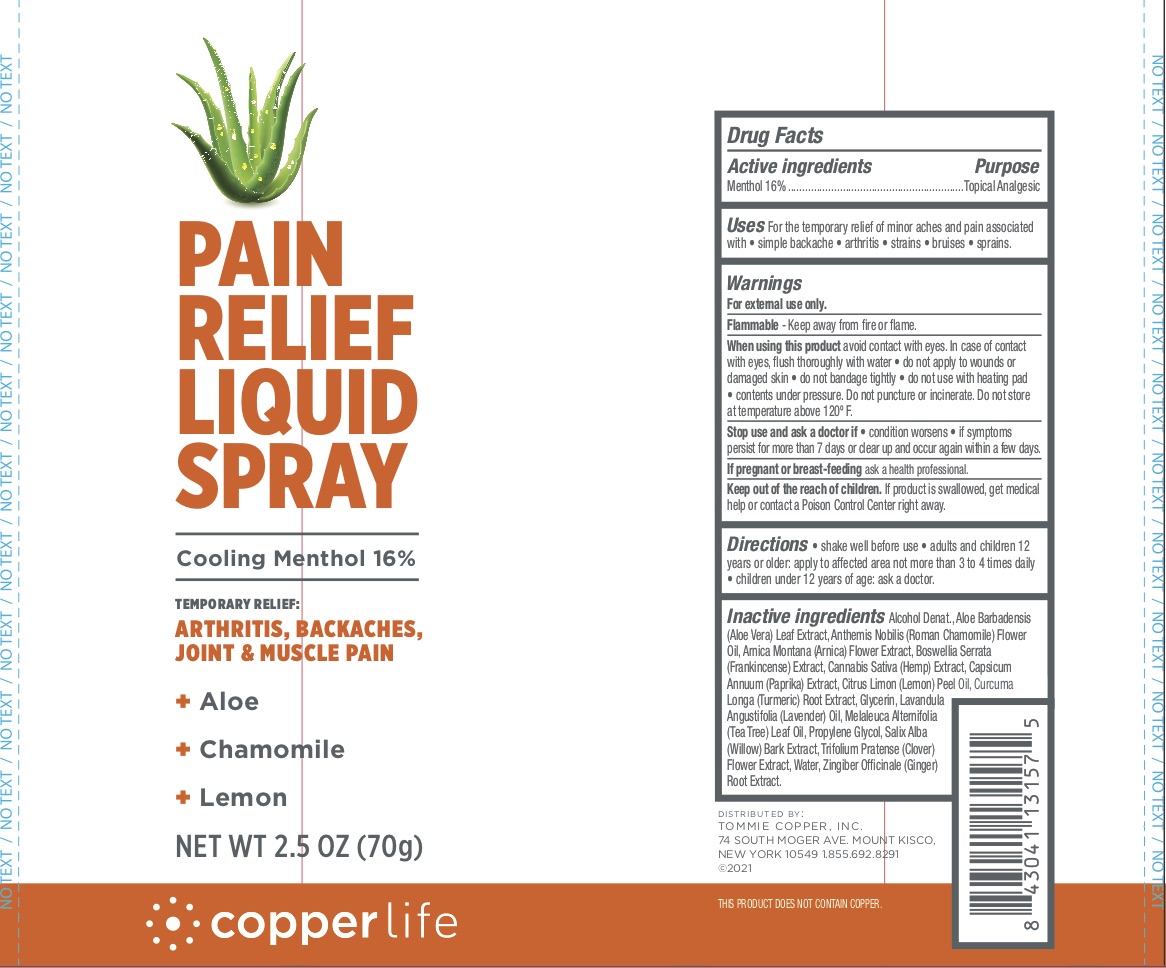 DRUG LABEL: Copperlife Pain Relief Liquid
NDC: 72562-121 | Form: SPRAY
Manufacturer: Tommie Copper, Inc.
Category: otc | Type: HUMAN OTC DRUG LABEL
Date: 20241215

ACTIVE INGREDIENTS: MENTHOL 16 g/100 g
INACTIVE INGREDIENTS: LAVENDER OIL; TEA TREE OIL; SALIX ALBA BARK; PROPYLENE GLYCOL; CALENDULA ARVENSIS LEAF; WATER; GLYCERIN; ALOE VERA LEAF; ALCOHOL; INDIAN FRANKINCENSE; CANNABIS SATIVA FLOWERING TOP; PAPRIKA; ARNICA MONTANA FLOWER; LEMON OIL, COLD PRESSED; CHAMAEMELUM NOBILE FLOWER OIL; TRIFOLIUM PRATENSE FLOWER; GINGER; TURMERIC

TC Pain Relief Liquid Spray

ACTIVE INGREDIENT

Menthol 16%

PURPOSE

Topical Analgesic

INDICATIONS AND USAGE

For the temporary relief of minor aches and pain associated with simple backaches, arthritis, strains, bruises, and sprains.

WARNINGS

For external use only. Flammable--Keep away from fire or flame. When using this product avoid contact with eyes. In case of contact with eyes, flush thoroughly with water, do not apply to wounds or damaged skin, and do not bandage tightly, do not use with a heating pad. Contents under pressure. Do not puncture or incinerate. Do not store at temperature above 120F. . Stop use and ask a doctor if condition worsens, if symptoms persist for more than 7 days or clear up and occur again within a few days.

PREGNANCY OR BREAST FEEDING

If pregnant or breast-feeding ask a health professional.

KEEP OUT OF REACH OF CHILDREN

If swallowed, get medical help or contact a Poison Control Center right away.

DOSAGE AND ADMINISTRATION

Shake well before use. Adults and children 12 years of age and older, apply to the affected area not more than 3 to 4 times daily. Children under 12 years of age: ask a doctor.

INACTIVE INGREDIENT

Alcohol Denat., Aloe Barbadensis (Aloe Vera) Leaf Extract, Anthemis Nobilis (Roman Chamomile) Flower Oil, Arnica Montana (Arnica) Flower Extract, Boswellia Serrata (Frankincense) Extract, Cannabis Sativa (Hemp) Extract, Capsicum Annuum (Paprika) Extract, Citrus Limon (Lemon) Peel Oil, Curcuma Longa (Tumeric) Root Extract, Glycerin, Lavandula Angustifolia (Lavender) Oil, Melaleuca Alternifolia (Tea Tree) Leaf Oil, Propylene Glycol, Salix Alba (Willow) Bark Extract, Trifolium Pratense (Clover) Flower Extract, Water, Zingiber Officinale (Ginger) Root Extract